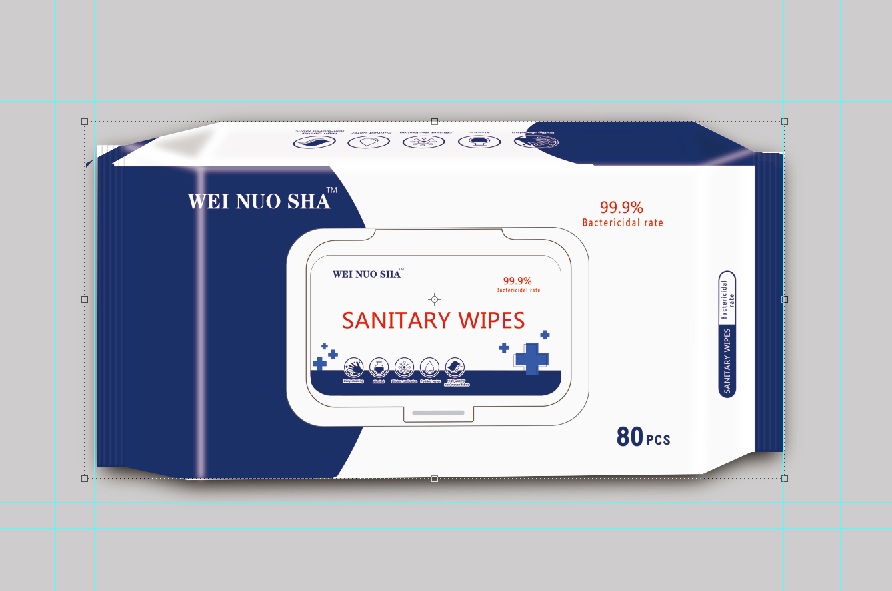 DRUG LABEL: Instant Hand Sanitizeing Wipe
NDC: 79539-601 | Form: CLOTH
Manufacturer: Shandong Yayun Sanitary Products Co., Ltd.
Category: otc | Type: HUMAN OTC DRUG LABEL
Date: 20231020

ACTIVE INGREDIENTS: BENZALKONIUM CHLORIDE 0.05 mg/100 1
INACTIVE INGREDIENTS: EDETATE DISODIUM ANHYDROUS; CHLORIDE ION; .ALPHA.-TOCOPHEROL ACETATE; PROPYLENE GLYCOL; GLYCERIN; PHENOXYETHANOL; WATER; CANANGA ODORATA LEAF OIL; ALOE VERA LEAF; SODIUM CITRATE; TEA TREE OIL

Instant Hand Sanitizeing Wipe

Instant Hand Sanitizeing Wipe

Active Ingredient(s)

Benzalkonium Chloride 0.05% w/w. Purpose: Antiseptic

Purpose

Antiseptic

Use

Instant Hand Sanitizeing Wipe to help reduce bacteria that potentially can cause disease. For use when soap and water are not available.

Warnings

For external use only.

Do not use

- in children less than 2 months of age
- on open skin wounds

When using this product keep out of eyes, ears, and mouth. In case of contact with eyes, rinse eyes thoroughly with water.
Stop use and ask a doctor if irritation or rash occurs. These may be signs of a serious condition.
Keep out of reach of children. If swallowed, get medical help or contact a Poison Control Center right away.

Stop use and ask a doctor if irritation or rash occurs. These may be signs of a serious condition.

Keep out of reach of children. If swallowed, get medical help or contact a Poison Control Center right away.

Directions

- Wipe the surface of the skin and let it dry naturally.
- Supervise children under 6 years of age when using this product to avoid swallowing.

Other information

- Store between 15-30C (59-86F)
- Avoid freezing and excessive heat above 40C (104F)

Inactive ingredients

Propylene Glycol
Aqua
Phenoxyethanol
Glycerin
Aloe Barbadensis leaf Extractt
Disodium EDTA
Getylpyridinium Chloride
Sodium Citrate
TocopherylAcetate
Tea tree oil
Perfum